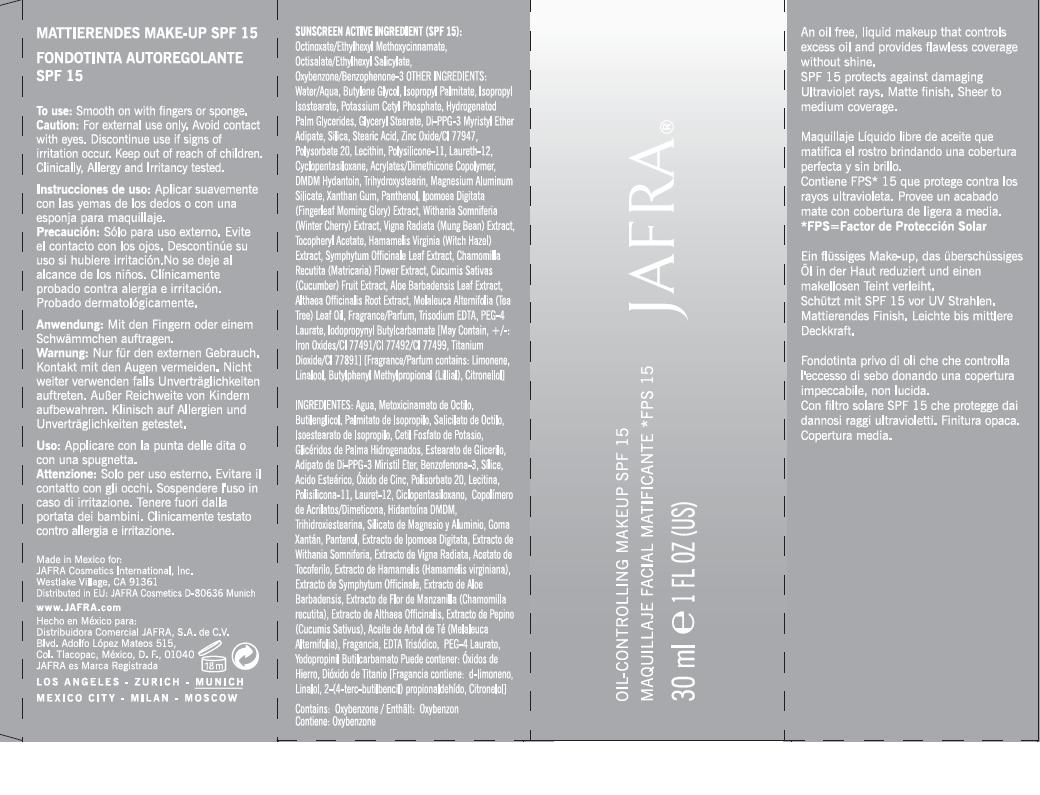 DRUG LABEL: OIL CONTROLLING MAKEUP
NDC: 68828-046 | Form: LOTION
Manufacturer: JAFRA COSMETICS INTERNATIONAL
Category: otc | Type: HUMAN OTC DRUG LABEL
Date: 20120427

ACTIVE INGREDIENTS: OCTINOXATE 6 g/100 mL; OCTISALATE 3 g/100 mL; OXYBENZONE 2 g/100 mL
INACTIVE INGREDIENTS: WATER; BUTYLENE GLYCOL; ISOPROPYL PALMITATE; ISOPROPYL ISOSTEARATE; POTASSIUM CETYL PHOSPHATE; HYDROGENATED PALM GLYCERIDES; GLYCERYL MONOSTEARATE; DI-PPG-3 MYRISTYL ETHER ADIPATE; SILICON DIOXIDE; STEARIC ACID; ZINC OXIDE; POLYSORBATE 20; LECITHIN, SOYBEAN; POLYSILICONE-15; LAURETH-12; CYCLOMETHICONE 5; CARBOMER INTERPOLYMER TYPE A (55000 MPA.S); DMDM HYDANTOIN; TRIHYDROXYSTEARIN; MAGNESIUM ALUMINUM SILICATE; XANTHAN GUM; PANTHENOL; IPOMOEA MAURITIANA TUBER; WITHANIA SOMNIFERA FLOWER; MUNG BEAN; ALPHA-TOCOPHEROL ACETATE; HAMAMELIS VIRGINIANA BARK; COMFREY LEAF; CHAMOMILE; CUCUMBER; ALOE VERA LEAF; ALTHAEA OFFICINALIS ROOT; TEA TREE OIL; EDETATE TRISODIUM; PEG-4 LAURATE; IODOPROPYNYL BUTYLCARBAMATE; FERRIC OXIDE RED; FERRIC OXIDE YELLOW; FERROSOFERRIC OXIDE; TITANIUM DIOXIDE

OIL CONTROLLING MAKEUP SPF-15

SUNSCREEN ACTIVE INGREDIENT (SPF 15):
OCTINOXATE/ETHYLHEXYL METHOXYCINNAMATE, OCTISALATE/ETHYLHEXYL SALICYLATE, OXYBENZONE/BENZOPHENONE-3

PURPOSE: SUNSCREEN

INACTIVE INGREDIENT

OTHER INGREDIENTS: WATER/AQUA, BUTYLENE GLYCOL, ISOPROPYL PALMITATE, ISOPROPYL ISOSTEARATE, POTASSIUM CETHYL PHOSPHATE, HYDROGENATED PALM GLYCERIDES, GLYCERYL STEARATE, DI-PPG-3 MYRISTYL ETHER ADIPATE, SILICA, STEARIC ACID, ZINC OXIDE/CI 77947, POLYSORBATE 20, LECITHIN, POLYSILICONE-11, LAURETH-12, CYCLOPENTASILOXANE, ACRYLATES/DIMETHICONE COPOLYMER, DMDM HYDANTOIN, TRIHYDROXYSTEARIN, MAGNESIUM ALUMINUM SILICATE, XANTHAN GUM, PANTHENOL, IPOMOEA DIGITATA (FINGERLEAF MORNING GLORY) EXTRACT, WITHANIA SOMNIFERIA (WINTER CHERRY) EXTRACT, VIGNA RADIATA (MUNG BEAN) EXTRACT, TOCOPHERYL ACETATE, HAMAMELIS VIRGINIA (WITCH HAZEL) EXTRACT, SYMPHYTUM OFFICINALIS LEAF EXTRACT, CHAMOMILLA RECUTITA (MATRICARIA) FLOWER EXTRACT, CUCUMIS SATIVAS (CUCUMBER) FRUIT EXTRACT, ALOE BARBADENSIS LEAF EXTRACT, ALTHAEA OFFICINALIS ROOT EXTRACT, MELALEUCA ALTERNIFOLIA (TEA TREE) LEAF OIL, FRAGRANCE/PARFUM, TRISODIUM EDTA, PEG-4 LAURATE, IODOPROPYNYL BUTYLCARBAMATE [MAY CONTAIN, +/-: IRON OXIDES/CI 77491/CI 77492/CI 77499, TITANIUM DIOXIDE/CI 77891] [FRAGRANCE/PARFUM CONTAINS: LIMONENE, LINALOOL, BUTYLPHENYL METHYLPROPIONAL (LILIAL), CITRONELLOL]

DESCRIPTION

AN OIL FREE, LIQUID MAKEUP THAT CONTROLS EXCESS OIL AND PROVIDES FLAWLESS COVERAGE WITHOUT SHINE.

INDICATIONS AND USAGE

SPF 15 PROTECTS AGAINST DAMAGING ULTRAVIOLET RAYS. MATTE FINISH. SHEER TO MEDIUM COVERAGE.

TO USE: SMOOTH ON WITH FINGERS OR SPONGE.

WARNINGS

CAUTION: FOR EXTERNAL USE ONLY. AVOID CONTACT WITH EYES.

DISCONTINUE USE IF SIGNS OF IRRITATION OCCUR.

KEEP OUT OF REACH OF CHILDREN.

OTHER SAFETY INFORMATION

CLINICALLY, ALLERGY AND IRRITANCY TESTED.

PACKAGE LABEL

JAFRA

OIL CONTROLLING MAKEUP SPF 15

30 ML / 1 FL OZ